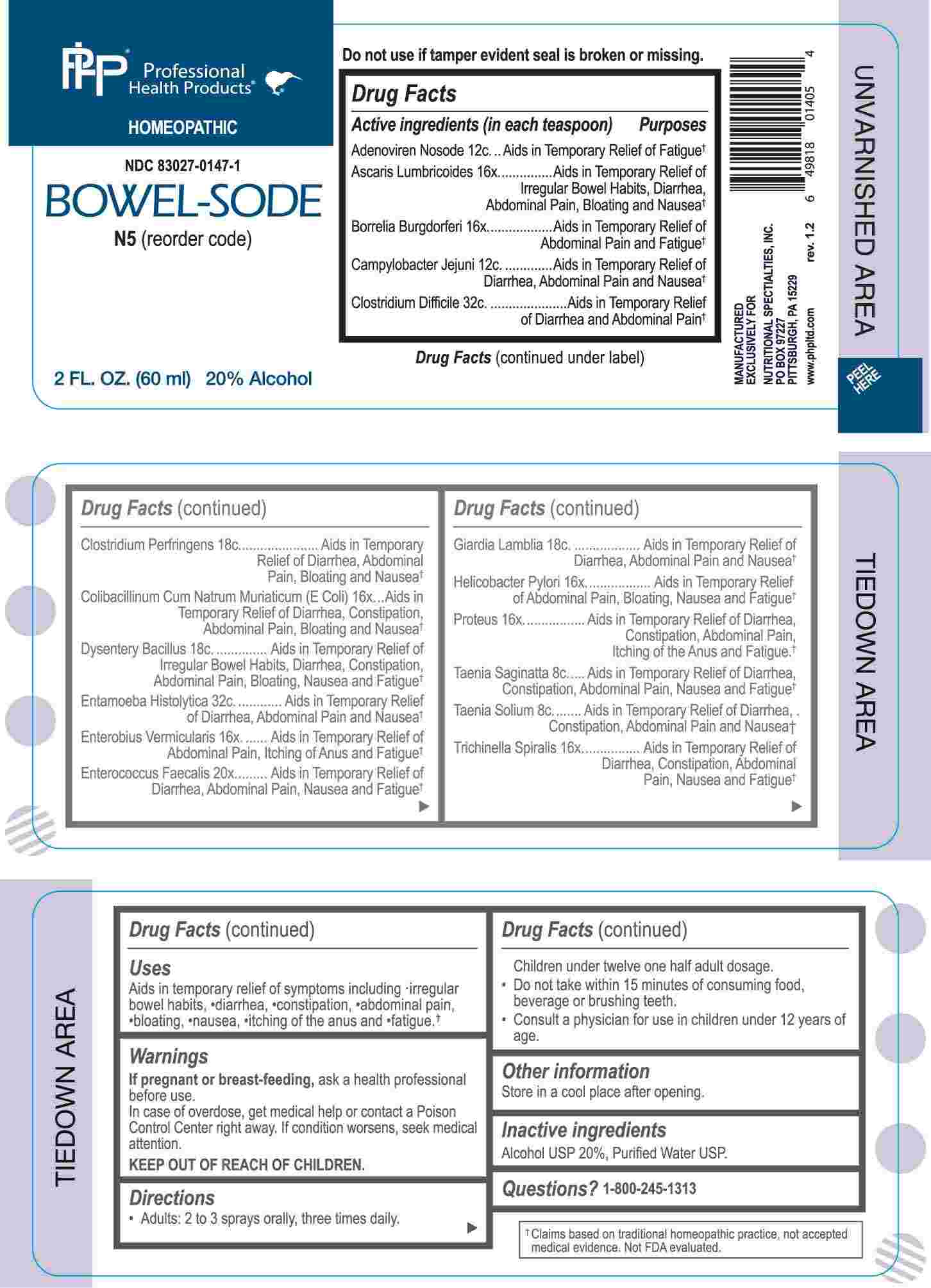 DRUG LABEL: Bowel Sode
NDC: 83027-0147 | Form: SPRAY
Manufacturer: Nutritional Specialties, Inc.
Category: homeopathic | Type: HUMAN OTC DRUG LABEL
Date: 20241112

ACTIVE INGREDIENTS: ASCARIS LUMBRICOIDES 16 [hp_X]/1 mL; BORRELIA BURGDORFERI 16 [hp_X]/1 mL; ESCHERICHIA COLI 16 [hp_X]/1 mL; ENTEROBIUS VERMICULARIS 16 [hp_X]/1 mL; HELICOBACTER PYLORI 16 [hp_X]/1 mL; PROTEUS VULGARIS 16 [hp_X]/1 mL; TRICHINELLA SPIRALIS 16 [hp_X]/1 mL; ENTEROCOCCUS FAECALIS 20 [hp_X]/1 mL; TAENIA SAGINATA 8 [hp_C]/1 mL; TAENIA SOLIUM 8 [hp_C]/1 mL; HUMAN ADENOVIRUS E SEROTYPE 4 STRAIN CL-68578 ANTIGEN 12 [hp_C]/1 mL; CAMPYLOBACTER JEJUNI 12 [hp_C]/1 mL; CLOSTRIDIUM PERFRINGENS 18 [hp_C]/1 mL; SHIGELLA DYSENTERIAE 18 [hp_C]/1 mL; GIARDIA LAMBLIA 18 [hp_C]/1 mL; CLOSTRIDIOIDES DIFFICILE 32 [hp_C]/1 mL; ENTAMOEBA HISTOLYTICA 32 [hp_C]/1 mL
INACTIVE INGREDIENTS: WATER; ALCOHOL

DRUG FACTS

ACTIVE INGREDIENTS:

(in each spray) Adenoviren Nosode 12C, Ascaris Lumbricoides 16X, Borrelia Burgdorferi 16X, Campylobacter Jejuni 12C, Clostridium Difficile 32C, Clostridium Perfringens 18C, Colibacillinum Cum Natrum Muriaticum (E Coli) 16X, Dysentery Bacillus 18C, Entamoeba Histolytica 32C, Enterobius Vermicularis 16X, Enterococcus Faecalis 20X, Giardia Lamblia 18C, Helicobacter Pylori 16X, Proteus 16X, Taenia Saginatta 8C, Taenia Solium 8C, Trichinella Spiralis 16X

PURPOSE:

Adenoviren Nosode – Aids in Temporary Relief of Fatigue,† Ascaris Lumbricoides – Aids in Temporary Relief of Irregular Bowel Habits, Diarrhea, Abdominal Pain, Bloating and Nausea,† Borrelia Burgdorferi – Aids in Temporary Relief of Abdominal Pain and Fatigue,† Campylobacter Jejuni – Aids in Temporary Relief of Diarrhea, Abdominal Pain and Nausea,† Clostridium Difficile – Aids in Temporary Relief of Diarrhea and Abdominal Pain,† Clostridium Perfringens – Aids in Temporary Relief of Diarrhea, Abdominal Pain, Bloating and Nausea,† Colibacillinum Cum Natrum Muriaticum (E Coli) – Aids in Temporary Relief of Diarrhea, Constipation, Abdominal Pain, Bloating and Nausea,† Dysentery Bacillus – Aids in Temporary Relief of Irregular Bowel Habits, Diarrhea, Constipation, Abdominal Pain, Bloating, Nausea and Fatigue,† Entamoeba Histolytica – Aids in Temporary Relief of Diarrhea, Abdominal Pain and Nausea,† Enterobius Vermicularis – Aids in Temporary Relief of Abdominal Pain, Itching of Anus and Fatigue,† Enterococcus Faecalis – Aids in Temporary Relief of Diarrhea, Abdominal Pain, Nausea and Fatigue,† Giardia Lamblia – Aids in Temporary Relief of Diarrhea, Abdominal Pain and Nausea,† Helicobacter Pylori – Aids in Temporary Relief of Abdominal Pain, Bloating, Nausea and Fatigue,† Proteus – Aids in Temporary Relief of Diarrhea, Constipation, Abdominal Pain, Itching of the Anus and Fatigue,† Taenia Saginatta – Aids in Temporary Relief of Diarrhea, Constipation, Abdominal Pain, Nausea and Fatigue,† Taenia Solium – Aids in Temporary Relief of Diarrhea, Constipation, Abdominal Pain and Nausea,† Trichinella Spiralis – Aids in Temporary Relief of Diarrhea, Constipation, Abdominal Pain, Nausea and Fatigue†

†Claims based on traditional homeopathic practice, not accepted medical evidence. Not FDA evaluated.

USES:

Aids in temporary relief of symptoms including •irregular bowel habits, •diarrhea, • constipation, • abdominal pain, •bloating, •nausea, •itching of the anus and •fatigue.†

†Claims based on traditional homeopathic practice, not accepted medical evidence. Not FDA evaluated.

WARNINGS:

If pregnant or breast-feeding, ask a health professional before use.

In case of overdose, get medical help or contact a Poison Control Center right away.

If condition worsens, seek medical attention.

KEEP OUT OF REACH OF CHILDREN

Do not use if tamper evident seal is broken or missing.

Store in a cool place after opening

KEEP OUT OF REACH OF CHILDREN:

In case of overdose, get medical help or contact a Poison Control Center right away.

DIRECTIONS:

• Adults: 2 to 3 sprays orally, three times daily. Children under twelve one half adult dosage.

• Do not take within 15 minutes of consuming food, beverage or brushing teeth.

• Consult a physician for use in children under 12 years of age.

INACTIVE INGREDIENTS:

Alcohol USP 20%, Purified Water USP.

QUESTIONS:

MANUFACTURED EXCLUSIVELY FOR

NUTRITIONAL SPECIALTIES, INC.

PO BOX 97227

PITTSBURG, PA 15229

www.phpltd.com

1-800-245-1313

PACKAGE LABEL DISPLAY:

Professional

Health Products

HOMEOPATHIC

NDC 83027-0147-1

BOWEL-SODE

2 FL. OZ (60 ml)